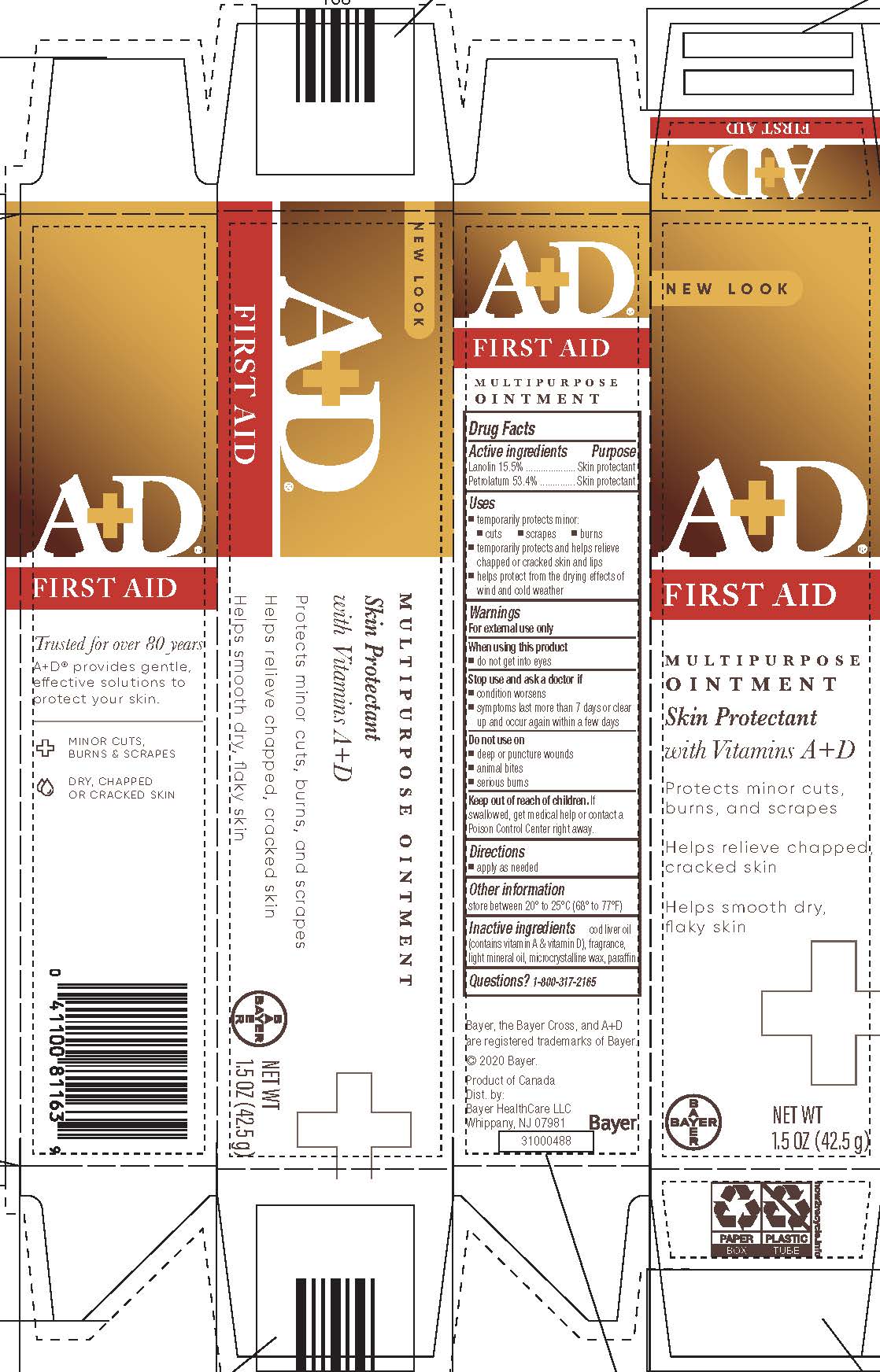 DRUG LABEL: A and D First Aid
NDC: 11523-7204 | Form: OINTMENT
Manufacturer: Bayer HealthCare LLC
Category: otc | Type: HUMAN OTC DRUG LABEL
Date: 20241206

ACTIVE INGREDIENTS: LANOLIN 136.4 mg/1 g; PETROLATUM 469.9 mg/1 g
INACTIVE INGREDIENTS: COD LIVER OIL; LIGHT MINERAL OIL; MICROCRYSTALLINE WAX; PARAFFIN

A+D® First Aid Ointment

Distributed by Bayer HealthCare LLC, Whippany, NJ, USA, 07981

Active Ingredients

Lanolin 15.5%, Petrolatum 53.4%

Purpose

Skin Protectant

Uses

- temporarily protects minor:
  - cuts
  - scrapes
  - burns
- temporarily protects and helps relieve chafed, chapped or cracked skin and lips
- helps protect from the drying effects of wind and cold weather

Warnings

For external use only

When using this product do not get into eyes

Stop use and ask a doctor if

- condition worsens
- symptoms last more than 7 days or clear up and occur again within a few days

Do not use on

- deep or puncture wounds
- animal bites
- serious burns

Keep out of reach of children. If swallowed, get medical help or contact a Poison Control Center right away.

Directions

apply as needed

Other information

store between 20°C to 25 °C (68° to 77°F)

Inactive Ingredients

cod liver oil (contains vitamin A & vitamin D), fragrance, light mineral oil, microcrystalline wax, paraffin

PRINCIPAL DISPLAY PANEL - 42.5 g Carton

New Look

A+D®
FIRST AID

MULTIPURPOSE

OINTMENT

with Vitamins A + D

Protects minor cuts

burns, and scrapes

Helps relieve chapped

cracked skin

helps smooth dry,

flaky skin

NET WT 1.5 OZ (42.5g)